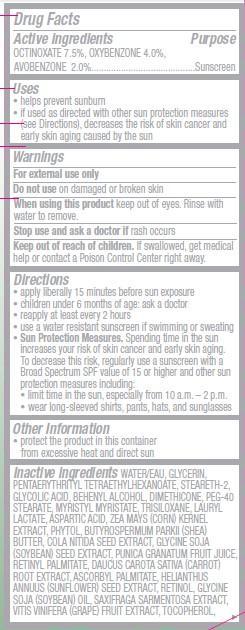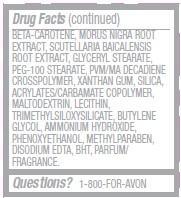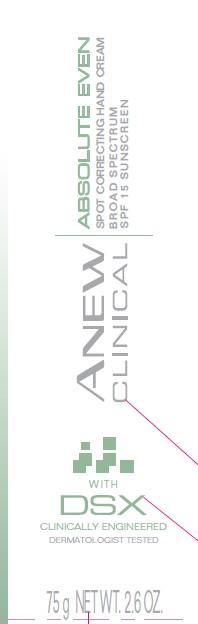 DRUG LABEL: Anew Clinical
NDC: 10096-0290 | Form: CREAM
Manufacturer: New Avon LLC
Category: otc | Type: HUMAN OTC DRUG LABEL
Date: 20160301

ACTIVE INGREDIENTS: octinoxate 75 mg/1 g; oxybenzone 40 mg/1 g; avobenzone 20 mg/1 g

Active ingredientsOCTINOXATE 7.5%, OXYBENZONE 4.0%,
AVOBENZONE 2.0%.......................

Purpose
................................Sunscreen

Uses
• helps prevent sunburn

• if used as directed with other sun protection measures (see Directions), decreases the risk of skin cancer and early skin aging caused by the sun

Warnings

For external use only.

Do not use on damaged or broken skin

When using this product keep out of eyes. Rinse with water to remove.

Stop use and ask a doctor if rash occurs

Keep out of reach of children. If swallowed, get medical help or contact a Poison Control Center right away.

Directions

• apply liberally 15 minutes before sun exposure
• children under 6 months of age: ask a doctor
• reapply at least every 2 hours
• use a water resistant sunscreen if swimming or sweating

• Sun Protection Measures. Spending time in the sun increases your risk of skin cancer and early skin aging. To decrease this risk, regularly use a sunscreen with a Broad Spectrum SPF value of 15 or higher and other sun protection measures including:

• limit time in the sun, especially from 10 a.m. – 2 p.m.
• wear long-sleeved shirts, pants, hats, and sunglasses

Other information

• protect the product in this container from excessive heat and direct sun

INACTIVE INGREDIENT

Inactive ingredients WATER/EAU, GLYCERIN, PENTAERYTHRITYL TETRAETHYLHEXANOATE, STEARETH-2, GLYCOLIC ACID, BEHENYL ALCOHOL, DIMETHICONE, PEG-40 STEARATE, MYRISTYL MYRISTATE, TRISILOXANE, LAURYL LACTATE, ASPARTIC ACID, ZEA MAYS (CORN) KERNEL EXTRACT, PHYTOL, BUTYROSPERMUM PARKII (SHEA) BUTTER, COLA NITIDA SEED EXTRACT, GLYCINE SOJA (SOYBEAN) SEED EXTRACT, PUNICA GRANATUM FRUIT JUICE, RETINYL PALMITATE, DAUCUS CAROTA SATIVA (CARROT) ROOT EXTRACT, ASCORBYL PALMITATE, HELIANTHUS ANNUUS (SUNFLOWER) SEED EXTRACT, RETINOL, GLYCINE SOJA (SOYBEAN) OIL, SAXIFRAGA SARMENTOSA EXTRACT, VITIS VINIFERA (GRAPE) FRUIT EXTRACT, TOCOPHEROL, BETA-CAROTENE, MORUS NIGRA ROOT EXTRACT, SCUTELLARIA BAICALENSIS ROOT EXTRACT, GLYCERYL STEARATE, PEG-100 STEARATE, PVM/MA DECADIENE CROSSPOLYMER, XANTHAN GUM, SILICA, ACRYLATES/CARBAMATE COPOLYMER, MALTODEXTRIN, LECITHIN, TRIMETHYLSILOXYSILICATE, BUTYLENE GLYCOL, AMMONIUM HYDROXIDE, PHENOXYETHANOL, METHYLPARABEN, DISODIUM EDTA, BHT, PARFUM/FRAGRANCE.

Questions? 1-800-FOR-AVON